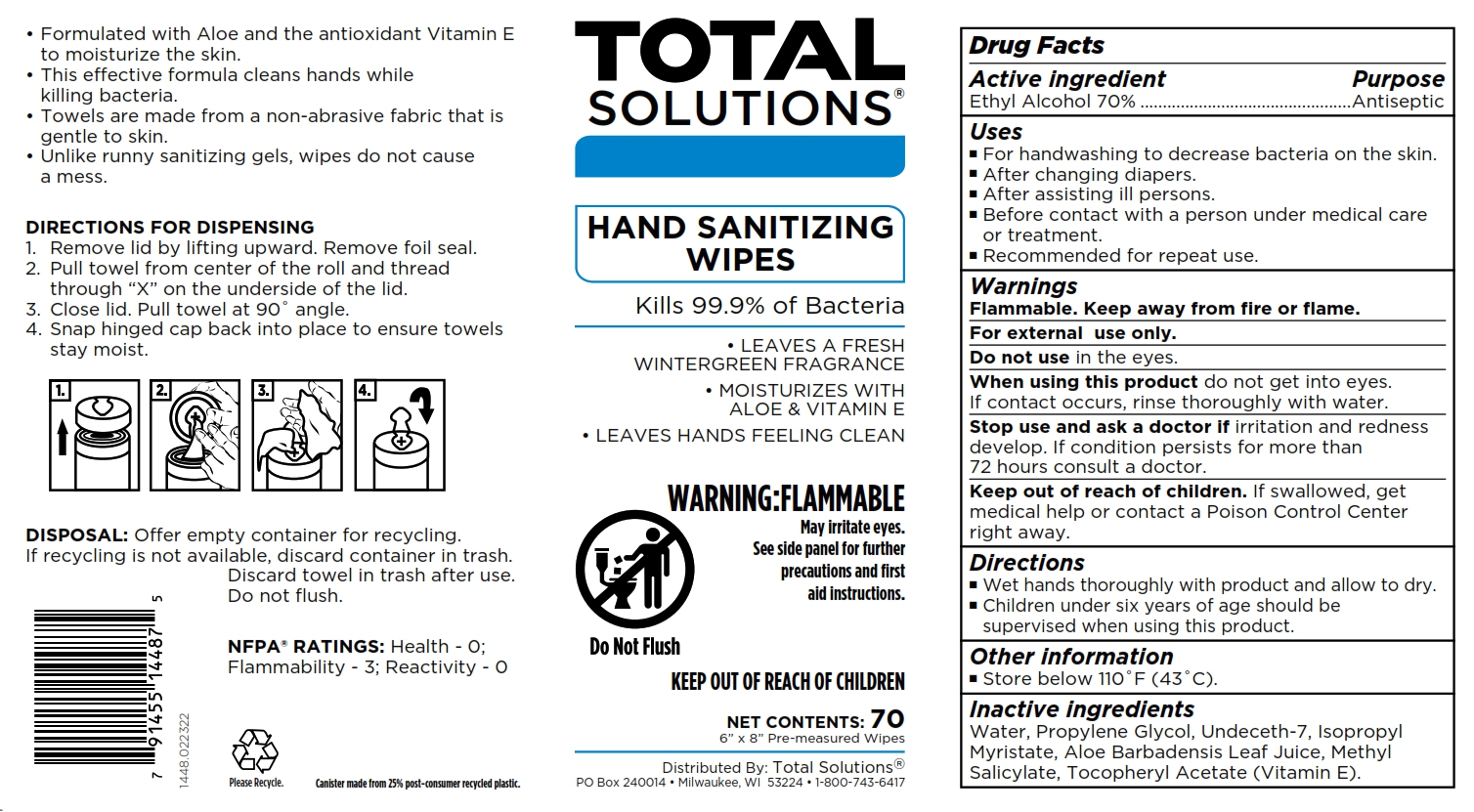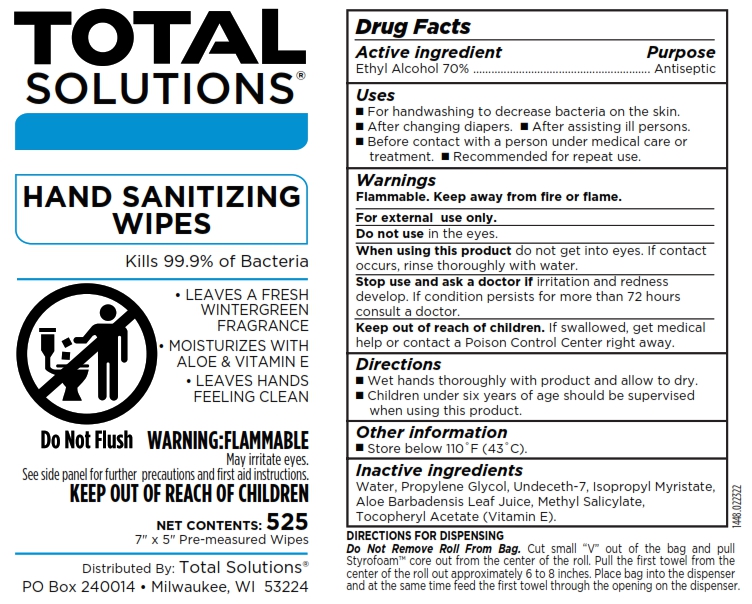 DRUG LABEL: Total Solutions Hand Sanitizing Wipes
NDC: 62819-448 | Form: CLOTH
Manufacturer: Athea Laboratories, Inc.
Category: otc | Type: HUMAN OTC DRUG LABEL
Date: 20250101

ACTIVE INGREDIENTS: ALCOHOL 70 g/100 g
INACTIVE INGREDIENTS: METHYL SALICYLATE; ALOE BARBADENSIS LEAF; ALPHA-TOCOPHEROL ACETATE; WATER; PROPYLENE GLYCOL; UNDECETH-7; ISOPROPYL MYRISTATE

1448-Total Solutions Hand Sanitizing Wipes

Active ingredient

Ethyl Alcohol 70%

Purpose

Antiseptic

Uses

- For handwashing to decrease bacteria on the skin.
- After changing diapers.
- After assisting ill persons.
- Before contact with a person under medical care or treatment.
- Recommended for repeat use.

Warnings

Flammable. Keep away from fire or flame.

For external use only.

Do not use

in the eyes.

When using this product

do not get into eyes. If contact occurs, rinse thoroughly with water.

Stop use and ask a doctor if

irritation and redness develop. If condition persists for more that 72 hours consult a doctor.

Keep out of reach of children

If swallowed, get medical help or contact a Poison Control Center right away.

Directions

- Wet hands thoroughly with product and allow to dry.
- Children under six years of age should be supervised when using this product.

Other information

- Store below 110 ºF (43º C).

Inactive ingredients

Water, Propylene Glycol, Undeceth-7, Isopropyl Myristate, Aloe Barbadensis Leaf Juice, Methyl Salicylate, Tocopheryl Acetate (Vitamin E).